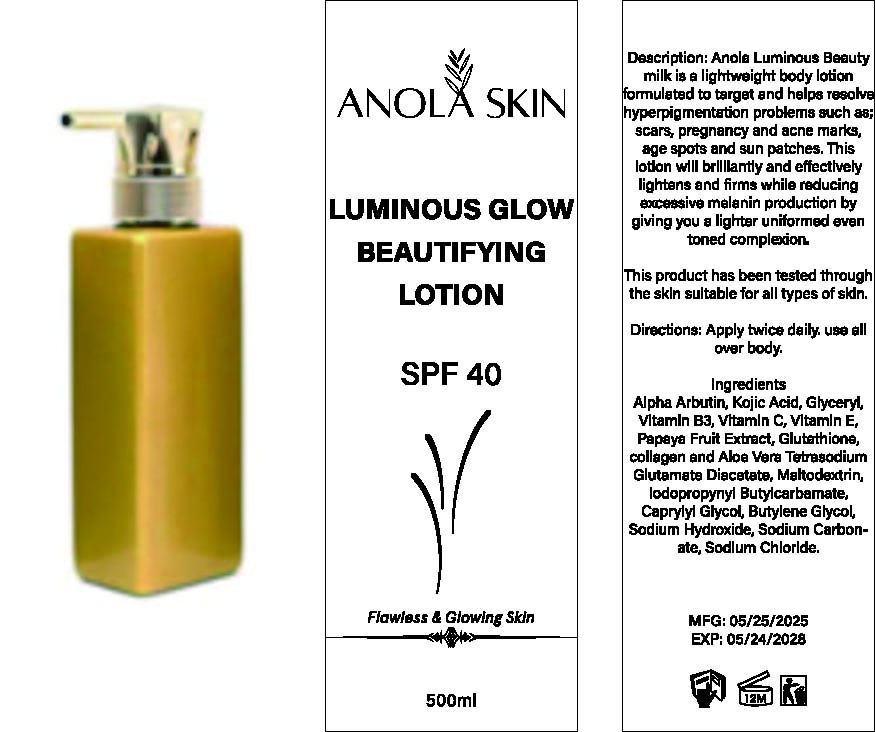 DRUG LABEL: LuminousGlowBeautifyingLotion
NDC: 84423-089 | Form: EMULSION
Manufacturer: Guangzhou Kadiya Biotechnology Co., Ltd.
Category: otc | Type: HUMAN OTC DRUG LABEL
Date: 20250803

ACTIVE INGREDIENTS: GLUTATHIONE 4 g/500 g; ARBUTIN 10 g/500 g; KOJIC ACID 15 g/500 g
INACTIVE INGREDIENTS: GLYCERYL RICINOLEATE; TETRASODIUM GLUTAMATE DIACETATE; SODIUM CARBONATE; PAPAYA; SODIUM HYDROXIDE; SODIUM CHLORIDE; NIACIN; BUTYLENE GLYCOL; ASCORBIC ACID; .ALPHA.-TOCOPHEROL; MALTODEXTRIN; IODOPROPYNYL BUTYLCARBAMATE; CAPRYLYL GLYCOL

PURPOSE

For facial skin cleansing, exfoliation and whitening moisturization

INACTIVE INGREDIENT

Glyceryl
Vitamin B3
Vitamin C
Vitamin E
Papaya Fruit Extract
Tetrasodium Glutamate Diacetate
Maltodextrin
lodopropynyl Butylcarbamate
Caprylyl Glycol
Butylene Glycol
Sodium Hydroxide
Sodium Carbonate
Sodium Chloride

Warning.

1、For external use only, avoid contact with eyes when used

2、Keep out of reach of children

INDICATIONS AND USAGE

Description: Anola Luminous Beauty milk is a lightweight body lotion formulated to target and helps resolve hyperpigmentation problems such as scars, pregnancy and acne marks, age spots and sun patches. This lotion will brilliantly and effectively lightens and firms while reducing excessive melanin production by giving you a lighter uniformed even toned complexion.

DOSAGE AND ADMINISTRATION

Apply twice daily, use all over body.

KEEP OUT OF REACH OF CHILDREN SECTION

Active Ingredients
Arbutine 2%
Kojic Acid3%
Glutathione0.8%

PACKAGE LABEL

Active Ingredients
Arbutine 2%
Kojic Acid3%
Glutathione0.8%

Uses：
For facial skin cleansing, exfoliation and whitening moisturization
The storage method：
Store sealed in a cool place and out of sunlight

Warning.
1、For external use only, avoid contact with eyes when used
2、Keep out of reach of children

Glyceryl
Vitamin B3
Vitamin C
Vitamin E
Papaya Fruit Extract
Tetrasodium Glutamate Diacetate
Maltodextrin
lodopropynyl Butylcarbamate
Caprylyl Glycol
Butylene Glycol
Sodium Hydroxide
Sodium Carbonate
Sodium Chloride